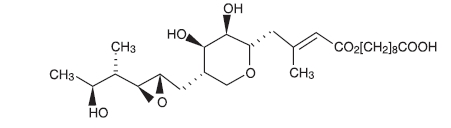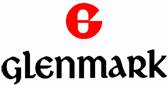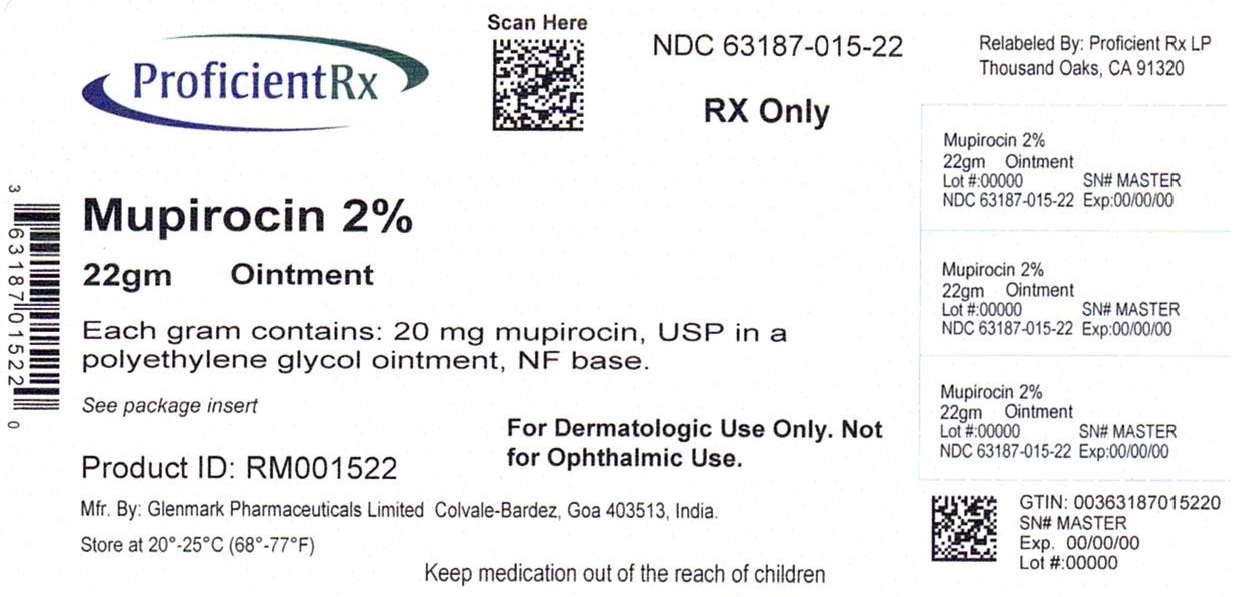 DRUG LABEL: Mupirocin
NDC: 63187-015 | Form: OINTMENT
Manufacturer: Proficient Rx LP
Category: prescription | Type: HUMAN PRESCRIPTION DRUG LABEL
Date: 20231101

ACTIVE INGREDIENTS: MUPIROCIN 20 mg/1 g
INACTIVE INGREDIENTS: POLYETHYLENE GLYCOL 400; POLYETHYLENE GLYCOL 3350

Mupirocin Ointment USP, 2%

For Dermatologic Use. Not for Ophthalmic Use

DESCRIPTION

Each gram of mupirocin ointment USP, 2% contains 20 mg mupirocin USP in a bland water miscible ointment base (polyethylene glycol ointment, N.F.) consisting of polyethylene glycol 400 and polyethylene glycol 3350. Mupirocin is a naturally occurring antibiotic. The chemical name is (E)-(2S, 3R,4R,5S)-5-[(2S,3S,4S,5S)-2,3-Epoxy-5-hydroxy-4-methylhexyl]tetrahydro-3,4-dihydroxy-β-methyl-2H-pyran-2-crotonic acid, ester with 9-hydroxynonanoic acid.

The molecular formula of mupirocin is C26H44O9, and the molecular weight is 500.63. The chemical structure is:

CLINICAL PHARMACOLOGY

Application of ^14C-labeled mupirocin ointment to the lower arm of normal male subjects followed by occlusion for 24 hours showed no measurable systemic absorption (<1.1 nanogram mupirocin per milliliter of whole blood). Measurable radioactivity was present in the stratum corneum of these subjects 72 hours after application.

Following intravenous or oral administration, mupirocin is rapidly metabolized. The principal metabolite, monic acid, is eliminated by renal excretion, and demonstrates no antibacterial activity. In a study conducted in 7 healthy adult male subjects, the elimination half-life after intravenous administration of mupirocin was 20 to 40 minutes for mupirocin and 30 to 80 minutes for monic acid. The pharmacokinetics of mupirocin has not been studied in individuals with renal insufficiency.

Microbiology:

Mupirocin is an antibacterial agent produced by fermentation using the organism Pseudomonas fluorescens. It is active against a wide range of gram-positive bacteria including methicillin-resistant Staphylococcus aureus (MRSA). It is also active against certain gram-negative bacteria. Mupirocin inhibits bacterial protein synthesis by reversibly and specifically binding to bacterial isoleucyl transfer-RNA synthetase. Due to unique mode of action, mupirocin demonstrates no in vitro cross-resistance with other classes of antimicrobial agents.

Resistance occurs rarely. However, when mupirocin resistance does occur, it appears to result from the production of a modified isoleucyl-tRNA synthetase. High-level plasmid-mediated resistance (MIC > 1024 mcg/mL) has been reported in some strains of S. aureus and coagulase-negative staphylococci.

Mupirocin is bactericidal at concentrations achieved by topical administration. However, the minimum bactericidal concentration (MBC) against relevant pathogens is generally 8-fold to 30-fold higher than the minimum inhibitory concentration (MIC). In addition, mupirocin is highly protein-bound (>97%), and the effect of wound secretions on the MICs of mupirocin has not been determined.

Mupirocin has been shown to be active against most strains of S. aureus and Streptococcus pyogenes,both in vitro and in clinical studies (see INDICATIONS AND USAGE).The following in vitro data are available, BUT THEIR CLINICAL SIGNIFICANCE IS UNKNOWN. Mupirocin is active against most strains of Staphylococcus epidermidis and Staphylococcus saprophyticus.

INDICATIONS AND USAGE

Mupirocin ointment USP, 2% is indicated for the topical treatment of impetigo due to: S. aureus and S. pyogenes.

CONTRAINDICATIONS

This drug is contraindicated in individuals with a history of sensitivity reactions to any of its components.

WARNINGS

Mupirocin ointment is not for ophthalmic use.

PRECAUTIONS

If a reaction suggesting sensitivity or chemical irritation should occur with the use of mupirocin ointment, treatment should be discontinued and appropriate alternative therapy for the infection instituted.

As with other antibacterial products, prolonged use may result in overgrowth of non-susceptible organisms, including fungi.

Mupirocin ointment is not formulated for use on mucosal surfaces. Intranasal use has been associated with isolated reports of stinging and drying. A paraffin-based formulation –*Bactroban® Nasal (mupirocin calcium ointment) – is available for intranasal use.

Polyethylene glycol can be absorbed from open wounds and damaged skin and is excreted by the kidneys. In common with other polyethylene glycol-based ointments, mupirocin ointment should not be used in conditions where absorption of large quantities of polyethylene glycol is possible, especially if there is evidence of moderate or severe renal impairment.

Information for Patients

Use this medication only as directed by your healthcare provider. It is for external use only. Avoid contact with the eyes. The medication should be stopped and your healthcare practitioner contacted if irritation, severe itching, or rash occurs.

If impetigo has not improved in 3 to 5 days, contact your healthcare practitioner.

Drug Interactions

The effect of the concurrent application of mupirocin ointment and other drug products has not been studied.

Carcinogenesis, Mutagenesis, Impairment of Fertility

Long-term studies in animals to evaluate carcinogenic potential of mupirocin have not been conducted.

Results of the following studies performed with mupirocin calcium or mupirocin sodium in vitroand in vivodid not indicate a potential for genotoxicity: Rat primary hepatocyte unscheduled DNA synthesis, sediment analysis for DNA strand breaks, Salmonella reversion test (Ames), Escherichia coli mutation assay, metaphase analysis of human lymphocytes, mouse lymphoma assay, and bone marrow micronuclei assay in mice.

Reproduction studies were performed in male and female rats with mupirocin administered subcutaneously at doses up to 14 times a human topical dose (approximately 60 mg mupirocin per day) on a mg/m^2 basis and revealed no evidence of impaired fertility and reproductive performance from mupirocin

Pregnancy

Teratogenic Effects

Reproduction studies have been performed in rats and rabbits with mupirocin administrated subcutaneously at doses up to 22 and 43 times, respectively, the human topical dose (approximately 60 mg mupirocin per day) on a mg/m^2 basis and revealed no evidence of harm to the fetus due to mupirocin. There are, however, no adequate and well-controlled studies in pregnant women. Because animal studies are not always predictive of human response, this drug should be used during pregnancy only if clearly needed.

Nursing Mothers

It is not known whether this drug is excreted in human milk. Because many drugs are excreted in human milk, caution should be exercised when mupirocin ointment is administered to a nursing woman.

Pediatric Use

The safety and effectiveness of mupirocin ointment have been established in the age range of 2 months to 16 years. Use of mupirocin ointment in these age groups is supported by evidence from adequate and well-controlled studies of mupirocin ointment in impetigo in pediatric patients studied as a part of the pivotal clinical trials (see CLINICAL STUDIES).

ADVERSE REACTIONS

The following local adverse reactions have been reported in connection with the use of mupirocin ointment : Burning, stinging, or pain in 1.5% of patients; itching in 1% of patients; rash, nausea, erythema, dry skin, tenderness, swelling, contact dermatitis, and increased exudate in less than 1% of patients. Systemic reactions to mupirocin ointment have occurred rarely.

DOSAGE AND ADMINISTRATION

A small amount of mupirocin ointment should be applied to the affected area 3 times daily. The area treated may be covered with a gauze dressing if desired. Patients not showing a clinical response within 3 to 5 days should be re-evaluated.

CLINICAL STUDIES

The efficacy of topical mupirocin ointment in impetigo was tested in 2 studies. In the first, patients with impetigo were randomized to receive either mupirocin ointment or vehicle placebo 3 times daily for 8 to 12 days. Clinical efficacy rates at end of therapy in the evaluable populations (adults and pediatric patients included) were 71% for mupirocin ointment (n = 49) and 35% for vehicle placebo (n = 51). Pathogen eradication rates in the evaluable populations were 94% for mupirocin ointment and 62% for vehicle placebo. There were no side effects reported in the group receiving mupirocin ointment.

In the second study, patients with impetigo were randomized to receive either mupirocin ointment 3 times daily or 30 to 40 mg/kg oral erythromycin ethylsuccinate per day (this was an unblinded study) for 8 days. There was a follow-up visit 1 week after treatment ended. Clinical efficacy rates at the follow-up visit in the evaluable populations (adults and pediatric patients included) were 93% for mupirocin ointment (n = 29) and 78.5% for erythromycin (n = 28). Pathogen eradication rates in the evaluable patient populations were 100% for both test groups. There were no side effects reported in the group receiving mupirocin ointment.

Pediatrics:

There were 91 pediatric patients aged 2 months to 15 years in the first study described above. Clinical efficacy rates at end of therapy in the evaluable populations were 78% for mupirocin ointment (n = 42) and 36% for vehicle placebo (n = 49). In the second study described above, all patients were pediatric except 2 adults in the group receiving mupirocin ointment. The age range of the pediatric patients was 7 months to 13 years. The clinical efficacy rate for mupirocin ointment (n = 27) was 96%, and for erythromycin it was unchanged (78.5%).

HOW SUPPLIED

Mupirocin ointment USP, 2% is supplied in 22 gram tubes.

NDC 63187-015-22 (22-gram tube)

Store at 20o to 25oC (68o to 77o F) [see USP Controlled Room Temperature].

*Bactroban® Nasal is a registered trademark of GlaxoSmithKline.

Manufactured by:

Glenmark Generics Ltd.
Colvale-Bardez, Goa 403 513, India

Manufactured for:

Glenmark Generics Inc., USA
Mahwah, NJ 07430

Questions? 1 (888)721-7115

www.glenmarkgenerics.com

Relabeled by:

Proficient Rx LP
Thousand Oaks, CA 91320

June 2011